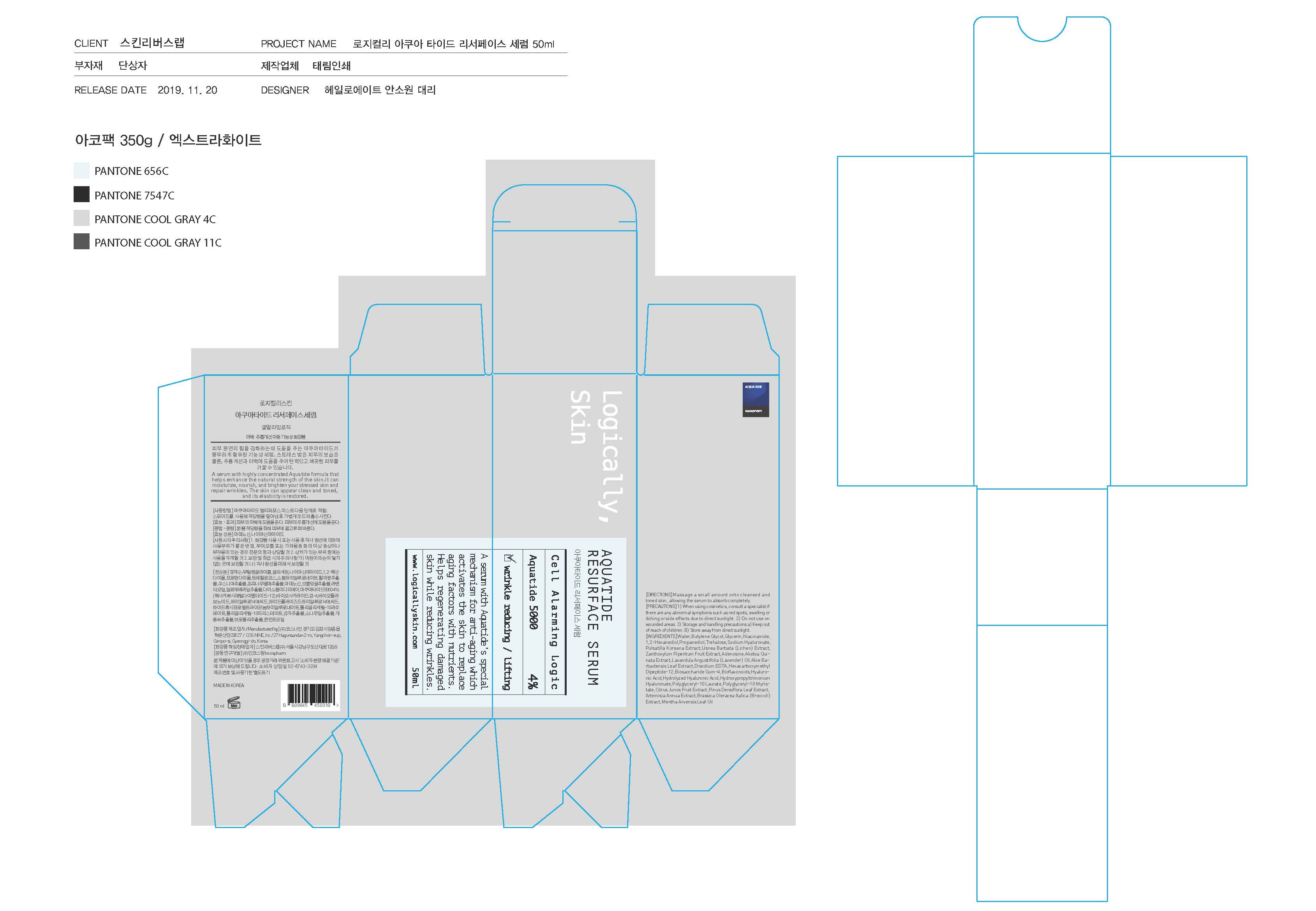 DRUG LABEL: AQUATIDE RESURFACE SERUM
NDC: 73330-0003 | Form: LIQUID
Manufacturer: COSNINE, Inc.
Category: otc | Type: HUMAN OTC DRUG LABEL
Date: 20191223

ACTIVE INGREDIENTS: NIACINAMIDE 2 g/100 mL; ADENOSINE 0.04 g/100 mL
INACTIVE INGREDIENTS: WATER; GLYCERIN

Drug Facts

ACTIVE INGREDIENT

adenosine, niacinamide

INACTIVE INGREDIENT

water, glycerin, butylene glycol, etc.

PURPOSE

A serum with highly concentrated Aquatide formula thathelps enhance the natural strength of the skin.It can moisturize, nourish, and brighten your stressed skin and repair wrinkles. The skin can appear clean and toned, and its elasticity is restored.

keep out of reach of the children

INDICATIONS AND USAGE

apply proper amount to the skin

WARNINGS

1. Do not use in the following cases(Eczema and scalp wounds)
2.Side Effects
1)Due to the use of this druf if rash, irritation, itching and symptopms of hypersnesitivity occur dicontinue use and consult your phamacisr or doctor
3.General Precautions
1)If in contact with the eyes, wash out thoroughty with water If the symptoms are servere, seek medical advice immediately
2)This product is for exeternal use only. Do not use for internal use
4.Storage and handling precautions
1)If possible, avoid direct sunlight and store in cool and area of low humidity
2)In order to maintain the quality of the product and avoid misuse
3)Avoid placing the product near fire and store out in reach of children

DOSAGE AND ADMINISTRATION

for external use only